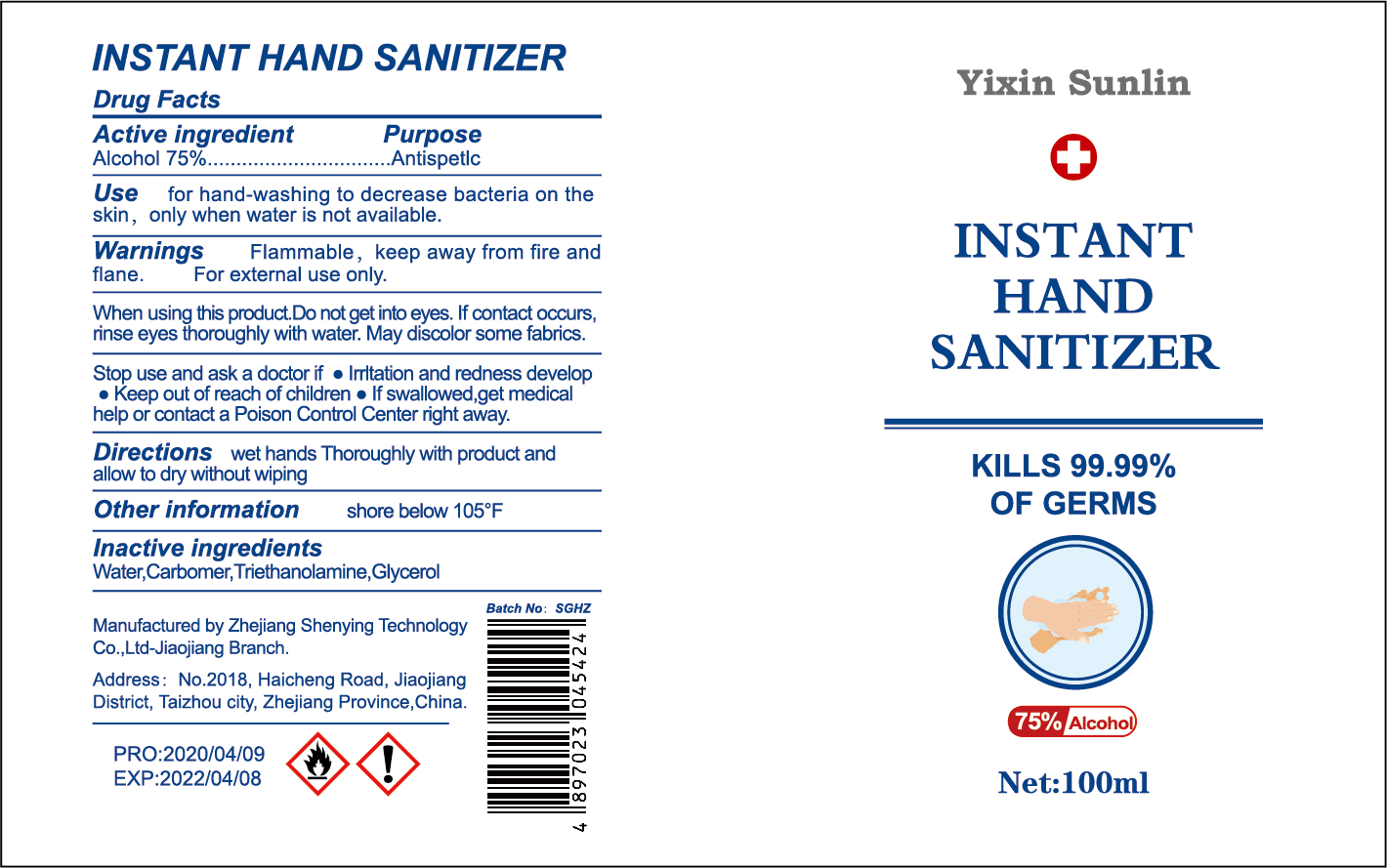 DRUG LABEL: Yixin Sunlin Instant Hand Sanitizer
NDC: 75112-001 | Form: GEL
Manufacturer: Zhejiang Shenying Technology Co., Ltd. Jiaojiang Branch
Category: otc | Type: HUMAN OTC DRUG LABEL
Date: 20201010

ACTIVE INGREDIENTS: ALCOHOL 75 mL/100 mL
INACTIVE INGREDIENTS: GLYCEROL FORMAL; CARBOMER 934; TRIETHANOLAMINE SULFATE

NA

Active Ingredient(s)

Alcohol 75% v/v. Purpose: Antiseptic

Purpose

Antiseptic

Use

For hand washing to decrease bacterial on the skin, only when water is not available

Warnings

Flammable. Keep away from fire and flame. For external use only.

When using this product, do not get into eyes. If contact occurs, rinse thoroughly with water. May discolor some fabrics

Stop use and ask a doctor if irritation and redness develops

Keep out of reach of children. If swallowed, get medical help or contact a Poison Control Center right away.

Directions

Wet hands thoroughly with product and allow to dry without wiping

Other information

Store below 105F

Inactive ingredients

Water, carbomer, triethanolamine, glycerol